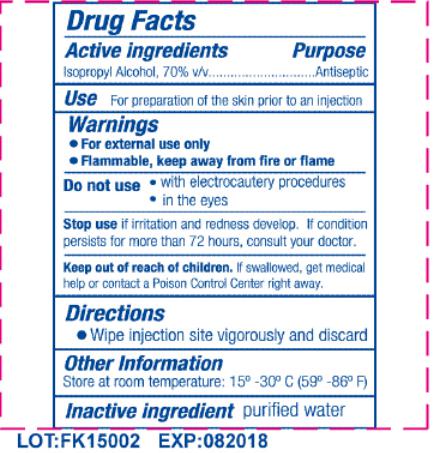 DRUG LABEL: Alcohol Pad
NDC: 80514-001 | Form: SWAB
Manufacturer: JIANGSU HAIDA INTERNATIONAL TRADING CO., LTD.
Category: otc | Type: HUMAN OTC DRUG LABEL
Date: 20231226

ACTIVE INGREDIENTS: ISOPROPYL ALCOHOL 0.7 mL/1 mL
INACTIVE INGREDIENTS: WATER

Active Ingredients

Isopropyl Alcohol USP, 70% v/v

Purpose

Antiseptic

Keep out of reach of children

If swallowed, get medical help or contact a Poison Control Center immediately.

Use

For preparation of the skin prior to an injection.

Warning

For external use only. Flammable, keep away from fire or flame.

Directions

Wipe injection site vigorously and discard.

Inactive ingredients

Purified water